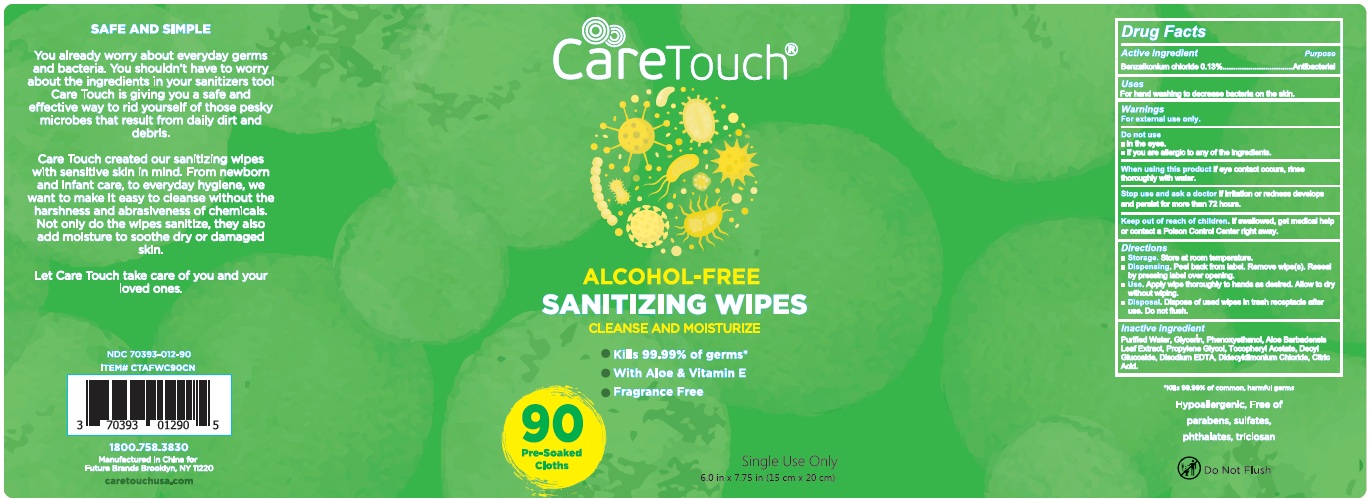 DRUG LABEL: Sanitizing Wipes
NDC: 75111-401 | Form: CLOTH
Manufacturer: Enping Jiaxin Daily Necessities Co., Ltd.
Category: otc | Type: HUMAN OTC DRUG LABEL
Date: 20200721

ACTIVE INGREDIENTS: BENZALKONIUM CHLORIDE 0.13 1/100 1
INACTIVE INGREDIENTS: PHENOXYETHANOL; GLYCERIN; WATER; ALOE VERA LEAF; PROPYLENE GLYCOL; .ALPHA.-TOCOPHEROL ACETATE; DECYL GLUCOSIDE; DIDECYLDIMONIUM CHLORIDE; CITRIC ACID MONOHYDRATE; EDETATE DISODIUM ANHYDROUS

Sanitizing Wipes

Active Ingredient(s)

Benzalkonium chloride 0.13mg/ml

Purpose: Antiseptic

Purpose

Antiseptic

Use

Sanitizing Wipes to help reduce bacteria that potentially can cause disease. For use when soap and water are not available.

Warnings

For external use only. Flammable. Keep away from heat or flame

Do not use

- in children less than 2 months of age
- on open skin wounds

When using this product keep out of eyes, ears, and mouth. In case of contact with eyes, rinse eyes thoroughly with water.
Stop use and ask a doctor if irritation or rash occurs. These may be signs of a serious condition.
Keep out of reach of children. If swallowed, get medical help or contact a Poison Control Center right away.

Stop use and ask a doctor if irritation or rash occurs. These may be signs of a serious condition.

Keep out of reach of children. If swallowed, get medical help or contact a Poison Control Center right away.

Directions

- Wipe the bady skin or other surface .
- Supervise children under 6 years of age when using this product to avoid swallowing.

Other information

- Store between 15-30C (59-86F)
- Avoid freezing and excessive heat above 40C (104F)

Inactive ingredients

Purified Water

Phenoxyethanol

Glycerin

Propylene Glycol

Aloe Barbadensis Leaf Extract

Tocopheryl Acetate

Decyl glucoside

Didecyldimonium Chloride

Citric Acid

Disodium EDTA